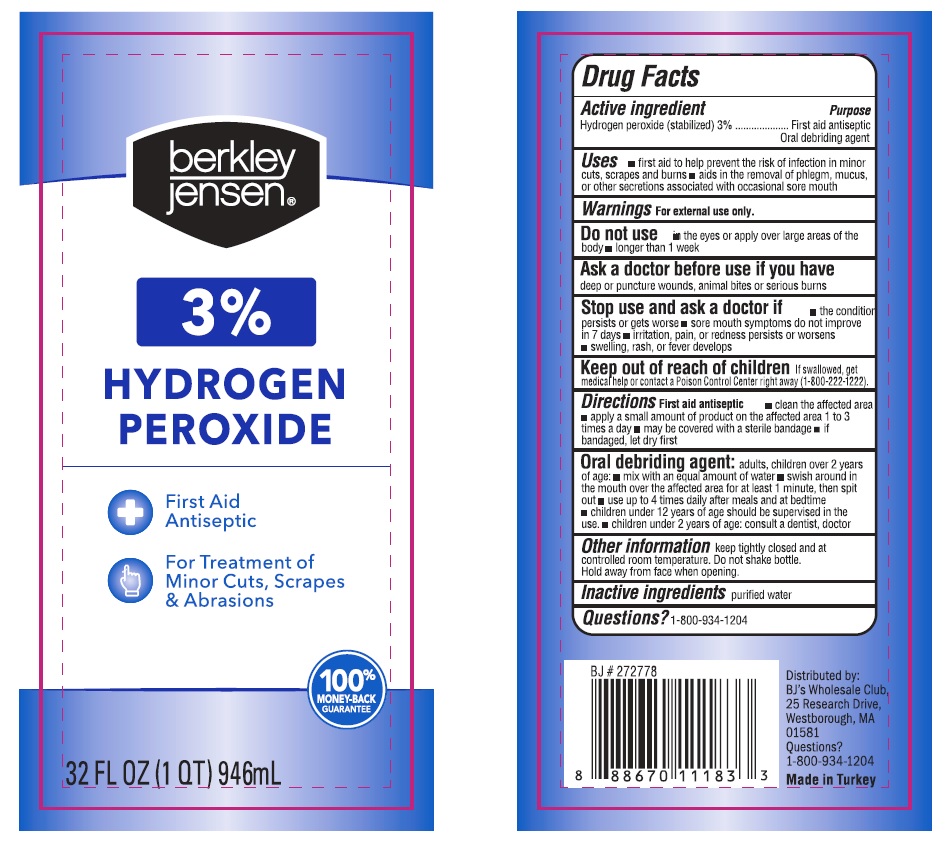 DRUG LABEL: Berkley Jensen
NDC: 76772-028 | Form: LIQUID
Manufacturer: TSM ITHALAT IHRACAT SANAYI VE DIS TICARET LIMITED SIRKETI
Category: otc | Type: HUMAN OTC DRUG LABEL
Date: 20210623

ACTIVE INGREDIENTS: HYDROGEN PEROXIDE 30 mg/1 mL
INACTIVE INGREDIENTS: WATER

Berkley Jensen 3% Hydrogen Peroxide

Active ingredient

Hydrogen peroxide 3%

Purpose

first aid antiseptic / oral debriding agent

INDICATIONS AND USAGE

Uses *First aid to help prevent the risk of infection in minor cuts, scrapes, and burns. *Aids in the removal of phlegm, mucus, or other secretions associated with occasional sore mouth.

Warnings

For external use only.

Ask a doctor before use if you have deep or puncture wounds, animal bites, or serious burns.

Stop use and ask a doctor if *swelling, rash, or fever develops. *the condition persists or gets worse. *sore mouth symptoms do not improve in 7 days. *irritation, pain or redness persists or worsens.

Keep out of reach of children. If swallowed, get medical help or contact poison control center right away.

stop use

Stop use and ask a doctor if *swelling, rash, or fever develops. *the condition persists or gets worse. *sore mouth symptoms do not improve in 7 days. *irritation, pain or redness persists or worsens.

Ask doctor

Ask a doctor before use if you have deep or puncture wounds, animal bites, or serious burns.

Do not use *in the eyes or apply over large areas of the body. *longer than one week.

DOSAGE AND ADMINISTRATION

Directions For use as a first aid antiseptic:

- Clean affected area.
- apply small amount of product on affected area 1-3 times a day.
- may be covered with a sterile bandage.
- For use as an oral debriding agent (oral rinse):
- adults and children 2 years of age and over
- mix with an equal amount of water.
- swish around in the mouth over affected area for at least 1 minute and then spit out. Do not swallow.
- use up to 4 times daily after meals and at bedtime or as directed by a dentist or doctor.
- children under 12 years should be supervised in the use of this product.
- children under 2 years of age: consult a dentist or doctor.

Other information

- Keep tightly closed and in a dark place at room temperature.
- Do not shake bottle. Hold away from face when opening.

Inactive ingredient purified water